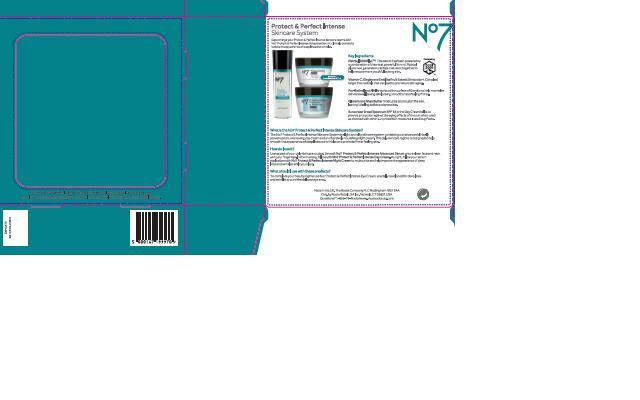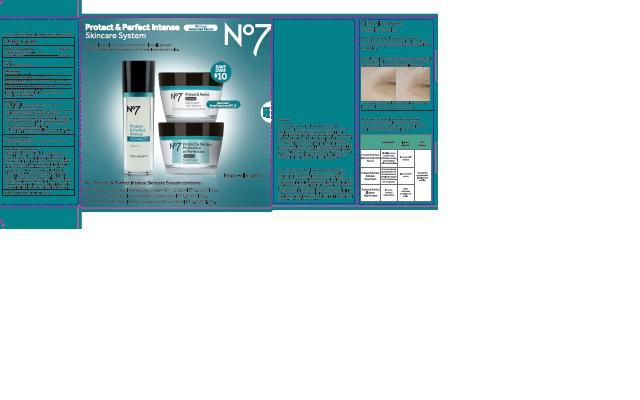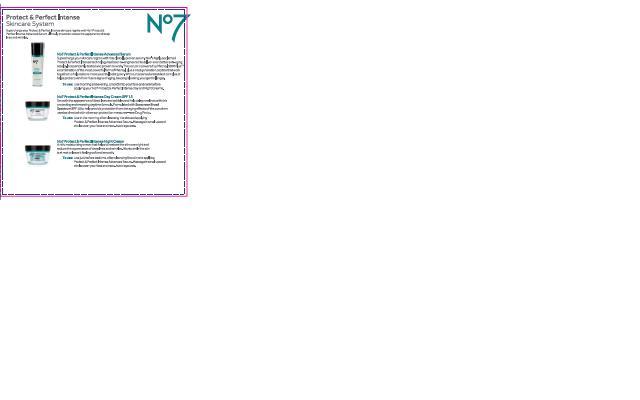 DRUG LABEL: No7 Protect and Perfect Intense Day Cream SPF 15
NDC: 11489-085 | Form: CREAM
Manufacturer: BCM Ltd
Category: otc | Type: HUMAN OTC DRUG LABEL
Date: 20140822

ACTIVE INGREDIENTS: AVOBENZONE 1.5 g/50 g; OCTOCRYLENE 2 g/50 g; OCTISALATE 1 g/50 g
INACTIVE INGREDIENTS: WATER; GLYCERIN; C12-15 ALKYL BENZOATE; DIMETHICONE; CETEARYL GLUCOSIDE; ALUMINUM STARCH OCTENYLSUCCINATE; TRIBEHENIN; AMMONIUM ACRYLOYLDIMETHYLTAURATE/VP COPOLYMER; PHENOXYETHANOL; ALCOHOL; SHEA BUTTER; POTASSIUM CETYL PHOSPHATE; BUTYLENE GLYCOL; METHYLPARABEN; ETHYLPARABEN; XANTHAN GUM; DIPROPYLENE GLYCOL; VITAMIN A PALMITATE; ASCORBYL GLUCOSIDE; HYALURONATE SODIUM; ALFALFA; EDETATE SODIUM; TERT-BUTYL ALCOHOL; LUPINUS ALBUS SEED; PHYLLANTHUS EMBLICA FRUIT; POLYSORBATE 20; POTASSIUM HYDROXIDE; GINKGO BILOBA LEAF OIL; ETHYLHEXYLGLYCERIN; TOCOPHEROL; PALMITOYL OLIGOPEPTIDE; PALMITOYL TETRAPEPTIDE-7

No7 Protect and Perfect Intense Day Cream SPF 15

Carton Active Ingredients Section

Active ingredients

Avobenzone 3%

Octisalate 2%

Octocrylene 4%

Uses

Uses - helps prevent sunburn

Warnings

For external use only

Do not use on damaged or broken skin

When using this product keep out of eyes. Rinse with water to remove.

Ask a doctor

Stop use and ask a doctor if rash occurs

Keep out of reach of children

If swallowed, get medical help or contact a Poison Control Center right away

Directions

Apply liberally 15 minutes before sun exposure

reapply at least every 2 hours

use a water resistnat sunscreen if swimming or sweating

children under 6 months of age: Ask a doctor

Sun Protection Measures. Spending time in the sun increases your risk of skin cancer and early skin aging.

To decrease this risk, regularly use a sunscreen with a Broad Spectrum SPF value of 15 or higher and other sun protection measures including:

Limit time in the sun, especially from 10 a.m - 2 p.m.

wear long-sleeved shirts,pants,hats and sunglasses.

Storage

Other information

Protect the product in this container from excessive heat and direct sun

Inactive ingredients

Aqua(Water), Glycerin, C12-15 alkyl benzoate, Dimethicone, Cetearyl glucoside, Aluminum starch octenylsuccinate, Tribehenin, Ammonium acryloydimethyltaurate/VP copolymer, phenoxyethanol, Alcohol denat., Butyrospermum parkii (Shea) butter, Potassium cetyl phosphate, Cetearyl alcohol, Butylene glycol, Dimethiconol, Methylparaben, Parfum(Fragrance), Xanthan gum, Ethylparaben, Dipropylene glycol, Retinyl palmitate, Ascorbyl glucoside, Sodium hyaluronate, Medicago sativa (Alfalfa) extract, Tetrasodium EDTA, T-butyl alcohol, Lupinus albus seed extract, Carbomer, Phyllanthus emblica fruit extract, Dimethylmethoxy chromanol, Polysorbate 20, Potassium hydroxide, Ginkgo biloba leaf extract, Ethylhexylglycerin, Silica, Tocopherol, Palmitoyl oligopepetide, Palmitoyl tetrapeptide-7.

PATIENT COUNSELING INFORMATION

Made in the UK

The Boots Company PLC Nottingham England NG2 3AA

Dist. by Boots Retail USA Inc. Norwalk CT 06851 USA

www.boots.com

Description

Protect and Perfect Intense Skincare System

Supercharge your Protect and Perfect Intense skincare regime with No7 Protect and Perfect Intense Advanced Serum, clinically proveen to reduce the appearance of deep lines and wrinkles.

Key Ingredients

Matrixyl 3000Plus TM. The serum has been powered by a combination of the most powerful form of Matrixyl plus a next generation peptide that work together to help restore more youthful looking skin.

Vitamin C, Gingko and Emblica Fruit Extract (Antioxidant Complex) target free radicals that can lead to premature skin aging.

Pro-Retinol and Alfalfa works at the surface of the skin to help normalize skin renewal, leaving skin looking smoother and feeling firmer.

Glycerin and Shea Butter moisturize and nourish the skin, leaving it feeling softer and smoother.

Sunscreen Broad Spectrum SPF 15 in the Day Cream helps to provide protection against the aging effects of the sun when used as directed with other sun protection measures - See Drug Facts.

What is the No7 Protect and Perfect Intense Skincare System?

The No7 Protect and Perfect Intense Skincare System is a light and silky skincare system containing our advanced clinically proven serum, a renewing day cream and an intensively nourishing night cream. This daily skicare regime is designed to help smooth the appearance of deep lines and wrinkles and promote firmer feeling skin.

How do I use it?

Use as part of your daily skincare routine. Smooth No7 Protect and Perfect Intense Advanced Serum onto a clean face and neck with your finger tips. In the morning, follow with No7 Protect and Perfect Intense Day Cream. At night, follow your serum application with No7 Protect and Perfect Intense Night Cream to moisturize and help improve the appearance of deep lines and wrinkles while you sleep.

What should I use with these products?

To complete your beauty rgime use No7 Protect and Perfect Intense Eye Cream, specially developed for deep lines and wrinkles around the delicate eye area.

Description

Protect and Perfect Intense Skincare System

Supercharge your Protect and Perfect Intense skincare regime with No7 Protect and Perfect Intense Advanced Serum, Clinically proven to reduce the appearance of deep lines and wrinkles.

No7 Protect and Perfect Intense Advanced Serum

Supercharge your skincare regime with this clinically proven serum. No7's highly acclaimed Protect and Perfect Intense Technology has been re-engineered to deliver even better anti-aging results. Independently tested and proven to work. This serum is powered by Matrixyl 3000PlusTM, a combination of the most powerful form of Matrixyl, plus a next generation peptide that work together to help restore more youthful looking skin. With our patented antioxidant complex, it helps protect skin from future signs of aging, keeping it looking younger for longer.

To use: Use morning and evening, smooth into your face and neck before applying your No7 Protect and Perfect Intense Day and Night Creams.

No7 Protect and Perfect Intense Day Cream SPF 15

Smooth the appearance of deep lines and wrinkles and help delay new lines with this protecting and renewing daytime formula. Formulated with Sunscreen Broad Spectrum SPF15 to help provide protection from the aging effects of the sun when used as directed with other sun protection measures - see Drug Facts.

To use: Use in the morning after cleansing the skin and applying Protect and Perfect Intense Serum. Massage in small upward circles over your face and neck. Avoid eye area.

No7 Protect and Perfect Intense Night Cream

A rich, moisturizing cream that helps to restore the skin overnight and reduce the appearance of deep lines and wrinkles. Works while the skin is at rest to leave it feeling soft and smooth.

To use: Use just before bedtime, after cleansing the skin and applying Protect and Perfect Intense Advanced Serum. Massage

in small upward circles over your face and neck. Avoid eye area.